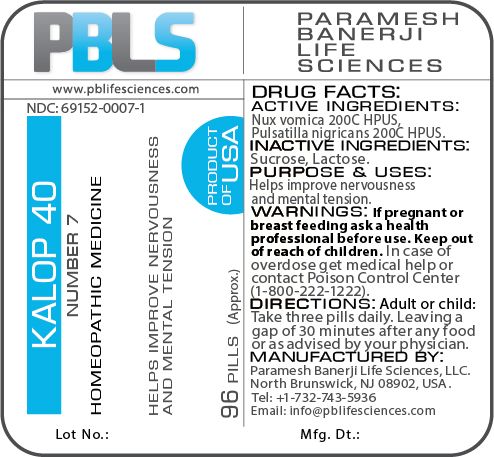 DRUG LABEL: Kalop 40 (Number 7)
NDC: 69152-0007 | Form: PELLET
Manufacturer: Paramesh Banerji Life Sciences LLC
Category: homeopathic | Type: HUMAN OTC DRUG LABEL
Date: 20180205

ACTIVE INGREDIENTS: PULSATILLA PRATENSIS 200 [hp_C]/1 1; STRYCHNOS NUX-VOMICA SEED 200 [hp_C]/1 1
INACTIVE INGREDIENTS: LACTOSE; SUCROSE

DRUG FACTS: Active Ingredients

Nux vomica 200C HPUS, Pulsatilla nigricans 200C HPUS

Inactive Ingredients

Sucrose, Lactose

Purpose

Helps improve nervousness and mental tension

Uses

Helps improve nervousness and mental tension

Warnings

If pregnant or breast feeding ask a health professional before use.

Keep out of reach of children. In case of overdose, get medical help or contact a Poison Control Center (1-800-222-1222) right away.

Direction

Adult or child: Take three pills daily. Leaving a gap of 30 minutes after any food or as advised by your physician.

Manufactured by

Paramesh Banerji Life Sciences, LLC.

North Brunswick, NJ 08902, USA.

Tel: +1-732-743-5936

Email: info@pblifesciences.com

Principal Display Panel

NDC: 69152-0007-1

Kalop 40

Number 7

Homeopathic Medicine

Helps improve nervousness and mental tension

96 Pills (Approx.)

Product of USA